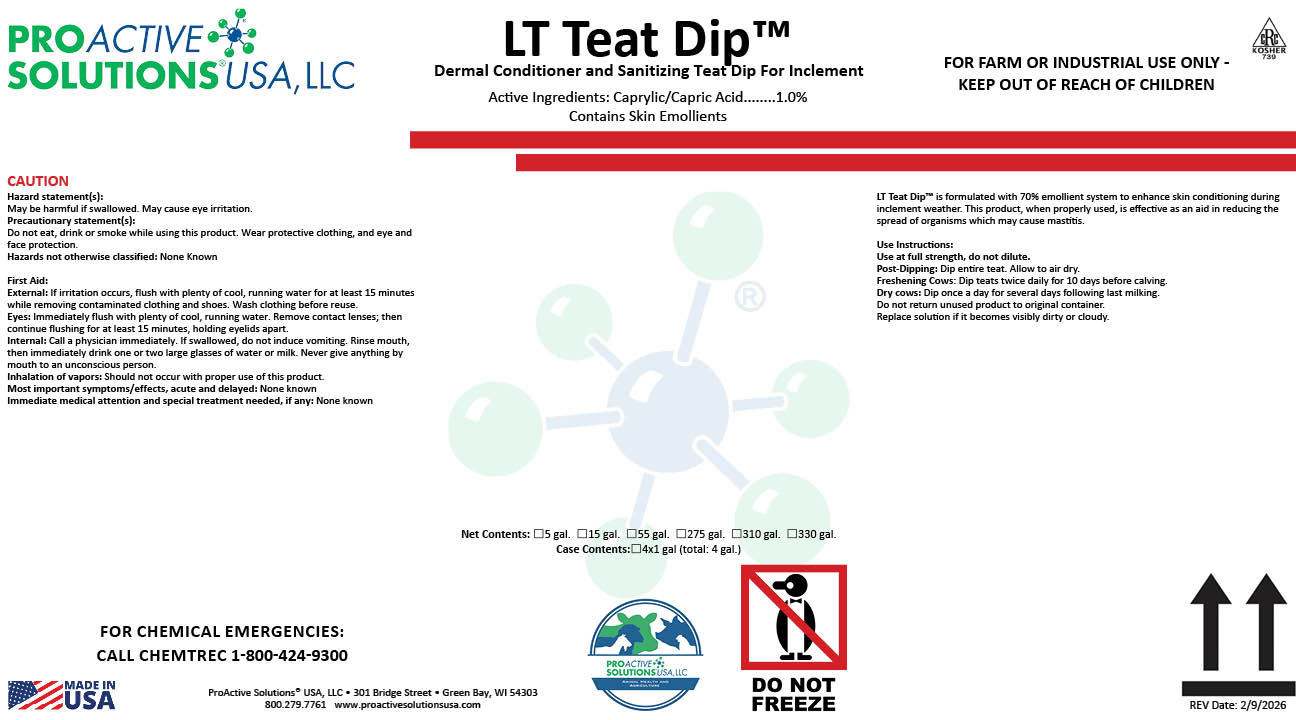 DRUG LABEL: LT Teat Dip
NDC: 63927-4285 | Form: LIQUID
Manufacturer: ProActive Solutions USA, LLC
Category: animal | Type: OTC ANIMAL DRUG LABEL
Date: 20260210

ACTIVE INGREDIENTS: CAPRYLIC/CAPRIC ACID 1 kg/100 kg

LT Teat Dip

LT Teat Dip™ is formulated with 70% emollient system to enhance skin conditioning during
inclement weather. This product, when properly used, is effective as an aid in reducing the
spread of organisms which may cause mastitis.
Use Instructions:
Use at full strength, do not dilute.
Post-Dipping: Dip entire teat. Allow to air dry.
Freshening Cows: Dip teats twice daily for 10 days before calving.
Dry cows: Dip once a day for several days following last milking.
Do not return unused product to original container.
Replace solution if it becomes visibly dirty or cloudy.

Hazard statement(s):
May be harmful if swallowed. May cause eye irritation.
Precautionary statement(s):
Do not eat, drink or smoke while using this product. Wear protective clothing, and eye and
face protection.
Hazards not otherwise classified: None Known
First Aid:
External: If irritation occurs, flush with plenty of cool, running water for at least 15 minutes
while removing contaminated clothing and shoes. Wash clothing before reuse.
Eyes: Immediately flush with plenty of cool, running water. Remove contact lenses; then
continue flushing for at least 15 minutes, holding eyelids apart.
Internal: Call a physician immediately. If swallowed, do not induce vomiting. Rinse mouth,
then immediately drink one or two large glasses of water or milk. Never give anything by
mouth to an unconscious person.
Inhalation of vapors: Should not occur with proper use of this product.
Most important symptoms/effects, acute and delayed: None known
Immediate medical attention and special treatment needed, if any: None known